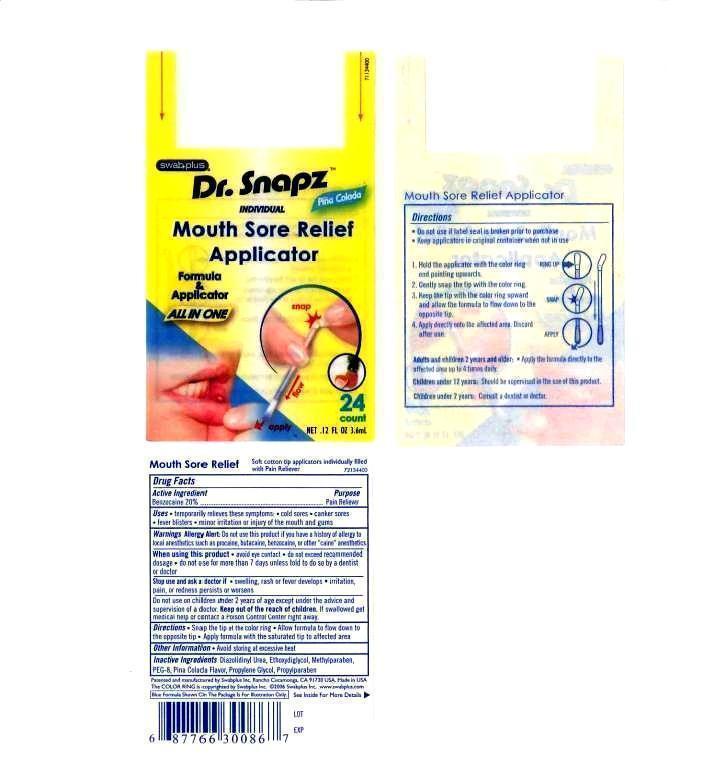 DRUG LABEL: Mouth Sore Relief Applicator
NDC: 65734-867 | Form: LIQUID
Manufacturer: Swabplus Inc.
Category: otc | Type: HUMAN OTC DRUG LABEL
Date: 20130214

ACTIVE INGREDIENTS: BENZOCAINE 200 mg/1 mL
INACTIVE INGREDIENTS: POLYETHYLENE GLYCOL 400; GLYCERIN; SACCHARIN SODIUM; WATER

Mouth Sore Relief Applicator

Drug fact

Active Ingredient

Benzocaine 20%

Purpose

Pain Reliever

Uses

temporarily relieves these symptoms. cold sores. scanker sores. fever blisters. minor irritation or injury of the mouth and gums.

Warning Allergy Alert

Do not use this product if you have a history of allergy to local anesthetics such as procaine, butacaine, benzocaine, or other "caine" anesthetics.

When using this product

avoid eye contact. do not exceed recommended dosage. do not use more than 7 days unless told to do so by a dentist or doctor.

Stop use and ask a doctor if

swelling. rash or fever develops, irritation, pain, or redness persists or worsen.

Do not use on children under 2 years except underteh advice and supervision of a doctor.

Keep out of the reach of children

if swallowed get medical help or contact a Poison Contro;mCenter right away.

Directions

Snap the tip at the color ring. Allow formula to flow down to the opposite tip. Apply formula with the saturated tip to affected area

Other Information

Avoid storaging at excessive heat.

Inactive Ingredient

Polyethylene glycol 400 (PEG-8), Glycerin, Saccharin sodium, water, pina Colada

Image of carton label